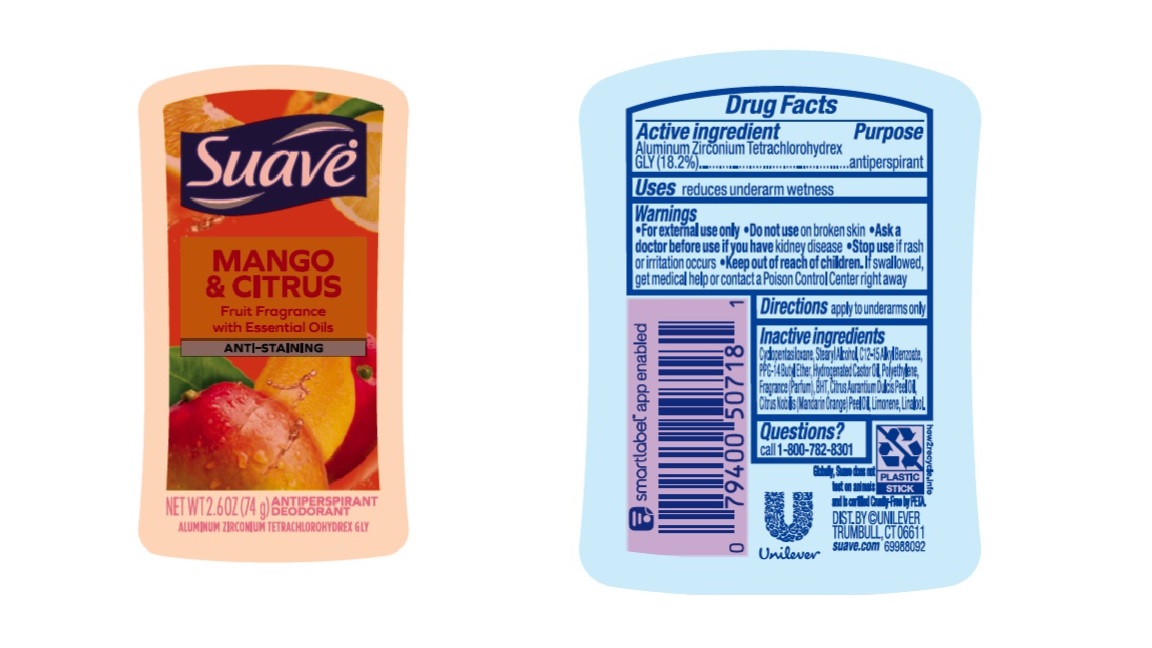 DRUG LABEL: Suave
NDC: 64942-2161 | Form: STICK
Manufacturer: Conopco Inc. d/b/a/ Unilever
Category: otc | Type: HUMAN OTC DRUG LABEL
Date: 20231010

ACTIVE INGREDIENTS: ALUMINUM ZIRCONIUM TETRACHLOROHYDREX GLY 18.2 g/100 g
INACTIVE INGREDIENTS: ALKYL (C12-15) BENZOATE; HIGH DENSITY POLYETHYLENE; HYDROGENATED CASTOR OIL; PPG-14 BUTYL ETHER; CYCLOMETHICONE 5; BUTYLATED HYDROXYTOLUENE; STEARYL ALCOHOL; LIMONENE, (+)-; LINALOOL, (+/-)-

Suave Mango & Citrus Anti-Staining Antiperspirant Deodorant

Drug Facts

Active ingredient

Aluminum Zirconium Tetrachlorohydrex GLY (18.2 %)

Purpose

antiperspirant

Uses

reduces underarm wetness

Warnings

• For externaluse only.
• Do not use on broken skin .
• Ask a doctor before use if you have kidney disease.
• Stop use if rash or irritation occurs.

• Keep out of reach of children.

If swallowed, get medical help or contact a Poison Control Center right away.

Directions

apply to underarms only

Inactive ingredients

Cyclopentasiloxane, Stearyl Alcohol, C12-15 Alkyl Benzoate, PPG-14 Butyl Ether, Hydrogenated Castor Oil, Fragrance (Parfum), Polyethylene, BHT, Citrus Aurantium Dulcis Peel Oil, Citrus Nobilis (Mandarin Orange) Peel Oil, Limonene, Linalool.

Questions?

Call 1-800-782-8301